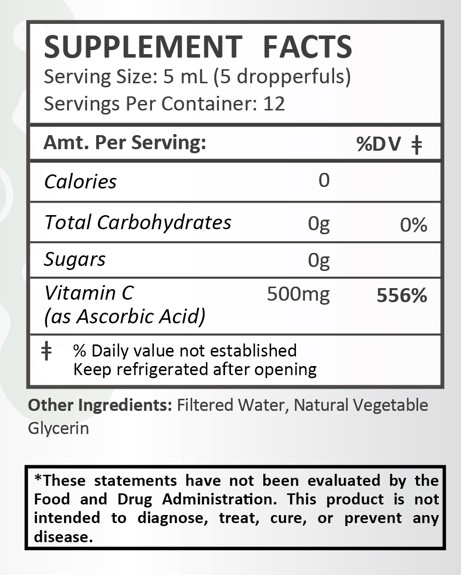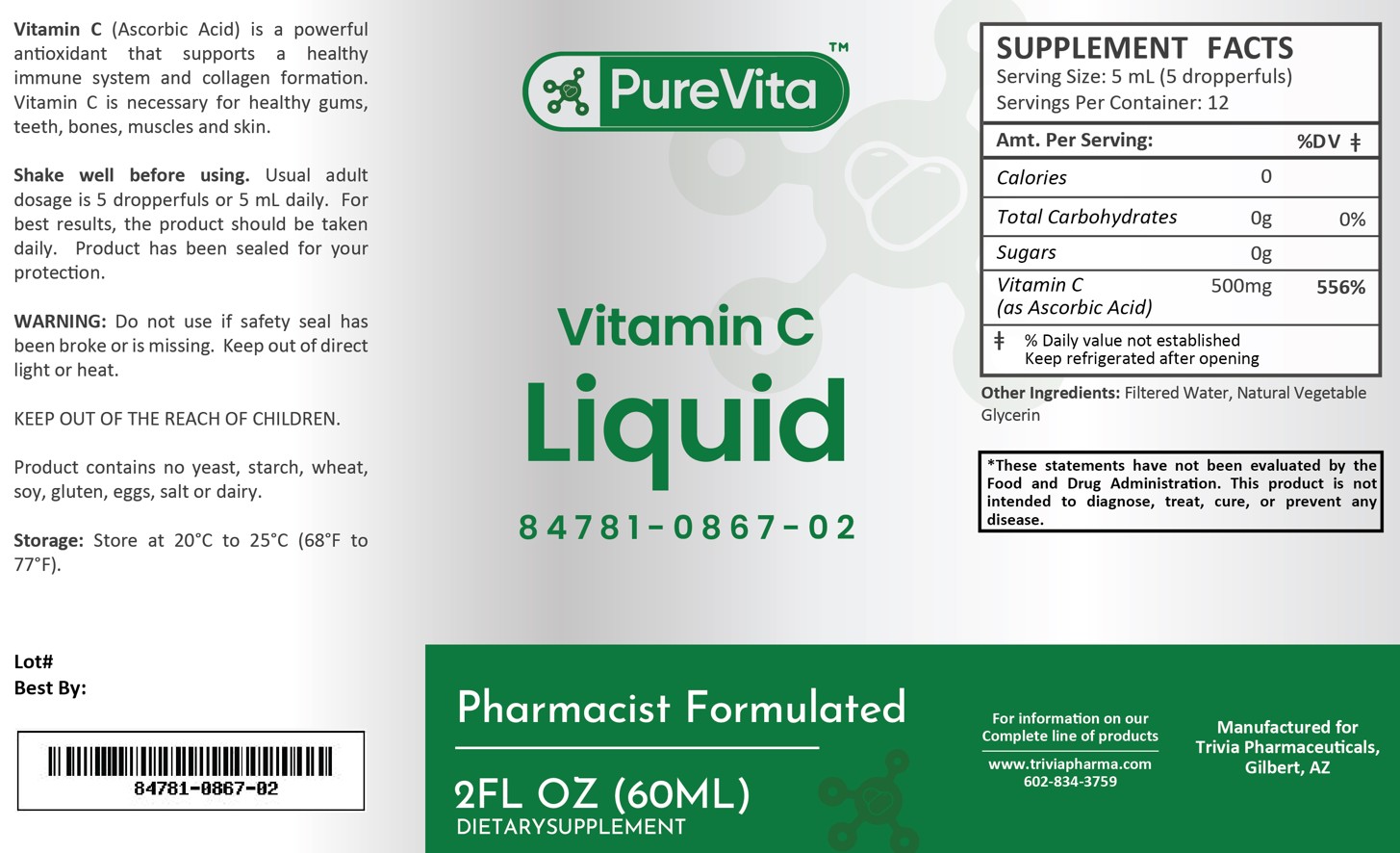 DRUG LABEL: PureVita Vitamin C
NDC: 84781-867 | Form: LIQUID
Manufacturer: Trivia Pharmaceuticals
Category: other | Type: Dietary Supplement
Date: 20250226

ACTIVE INGREDIENTS: ASCORBIC ACID 500 mg/5 mL

PureVita Vitamin C

Health Claim:

Vitamin C 500 mg/5 mL Dropper

Description:

PureVita Vitamin C Liquid is a powerful antioxidant that supports a healthy immune system and collage formation. Vitamin is necessary for health gums, teeth, bones, muscles and skin.

This listed product is not a National Drug Code, but instead has merely been formatted to comply with standard industry practice for pharmacy and insurance computer systems.

Warnings:

Do not use if safety seal has been broken or is missing. Keep out of direct light or heat.

KEEP OUT OF THE REACH OF CHILDREN.

Product contains no yeast, starch, wheat, soy, gluten, eggs, salt or dairy.

Dosage and Adminsitration:

Usual adult dose is 5 dropperfuls or 5 mL daily. For the best results, the product should be taken daily. Product has been sealed for your protection.

How Supplied:

PureVita Vitamin C Liquid is supplied as clear, white liquid

84781-0867-02

Reserved for Professional Recommendation

All prescriptions using this product shall be pursuant to state statutes as applicable. This is not an Orange Book product. There are no implied or explicit claims on therapeutic equivalence.

Manufactured for:
Trivia Pharmaceuticals

Gilbert, AZ

Storage:

Storage: Store at 20oC to 25oC (68oF to 77oF). Keep refrigerated after opening.